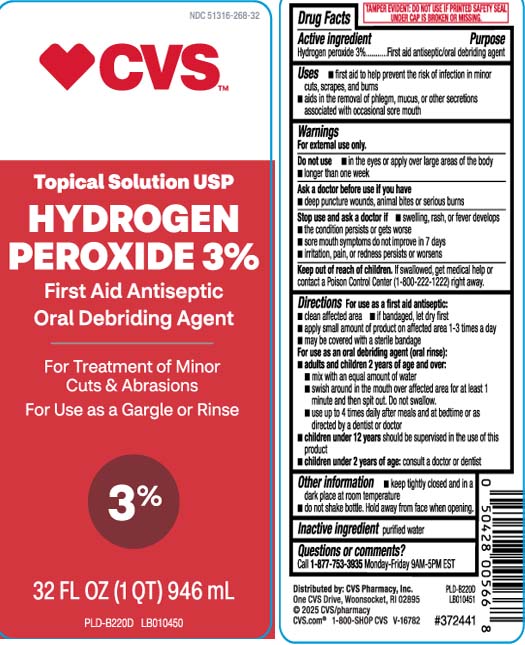 DRUG LABEL: Hydrogen Peroxide
NDC: 51316-268 | Form: LIQUID
Manufacturer: CVS PHARMACY, INC
Category: otc | Type: HUMAN OTC DRUG LABEL
Date: 20251217

ACTIVE INGREDIENTS: HYDROGEN PEROXIDE 3 mL/100 mL
INACTIVE INGREDIENTS: WATER

Drug Facts

Active ingredient

Hydrogen peroxide 3%

Purpose

First aid antiseptic/oral debriding agent

Uses

- first aid to help prevent the risk of infection in minor cuts, scrapes, and burns
- aids in the removal of phlegm, mucus, or other secretions associated with occasional sore mouth

Warnings

For external use only.

Do not use

- in the eyes or apply over large areas of the body
- longer than one week

Ask a doctor before use if you have

- deep puncture wounds, animal bites or serious burns

Stop use and ask a doctor if

- swelling, rash, or fever develops
- the condition persists or gets worse
- sore mouth symptoms do not improve in 7 days
- irritation, pain, or redness persists or worsens

Keep out of reach of children.

If swallowed, get medical help or contact a Poison Control Center (1-800-222-1222) right away.

Directions

For use as a first aid antiseptic:

- clean affected area
- if bandaged, let dry first
- apply small amount if product on affected area 1-3 times a day
- may be covered with a sterile bandage

For use as an oral debriding agent (oral rinse):

- adults and children 2 years of age and over:
  - mix with an equal amount of water
  - swish around in the mouth over affected area for at least 1 minute and then spit it out. Do not swallow.
  - use up to 4 times daily after meals and at bedtime or as directed by a dentist or doctor
- children under 12 years should be supervised in the use of this product
- children under 2 years of age: consult a doctor or dentist

Other information

- keep tightly closed and in a dark place at room temperature
- do not shake bottle. Hold away from face when opening

Inactive ingredient

purified water

Questions or comments?

Call 1-877-753-3935 Monday-Friday 9AM-5PM EST

Principal Display Panel

Topical Solution USP

Hydrogen Peroxide 3%

FIRST Aid Antiseptic

Oral Debriding Agent

For treatment of minor cuts & abrasions

For use as a gargle or rinse

FL OZ (mL)

TAMPER EVIDENT: DO NOT USE IF PRINTED SAFETY SEAL UNDER CAP IS BROKEN OR MISSING.

Distributed by: CVS Pharmacy, Inc.

One CVS Drive, Woonsocket, RI 02895

Package Label

CVS Hydrogen Peroxide 3%